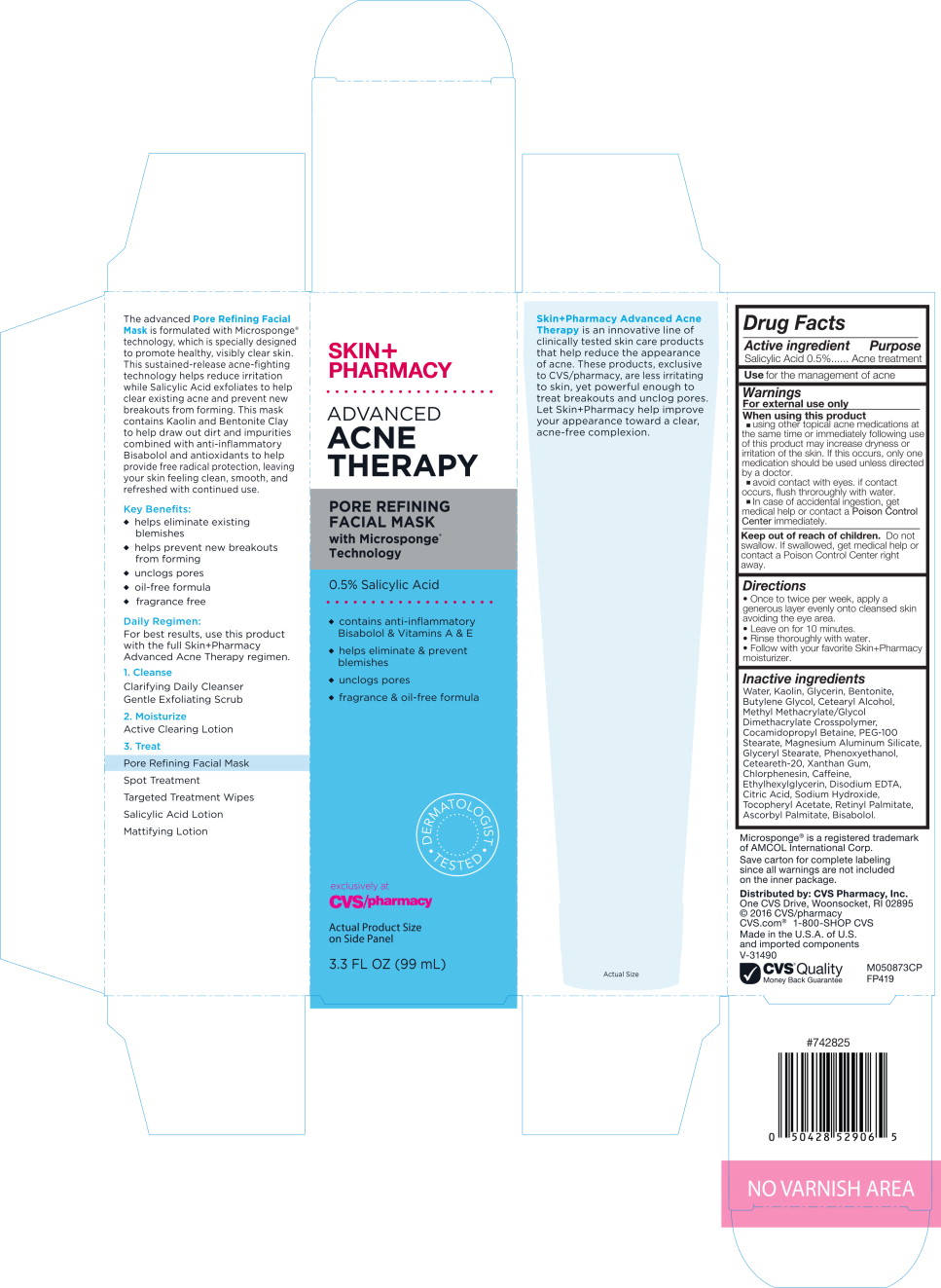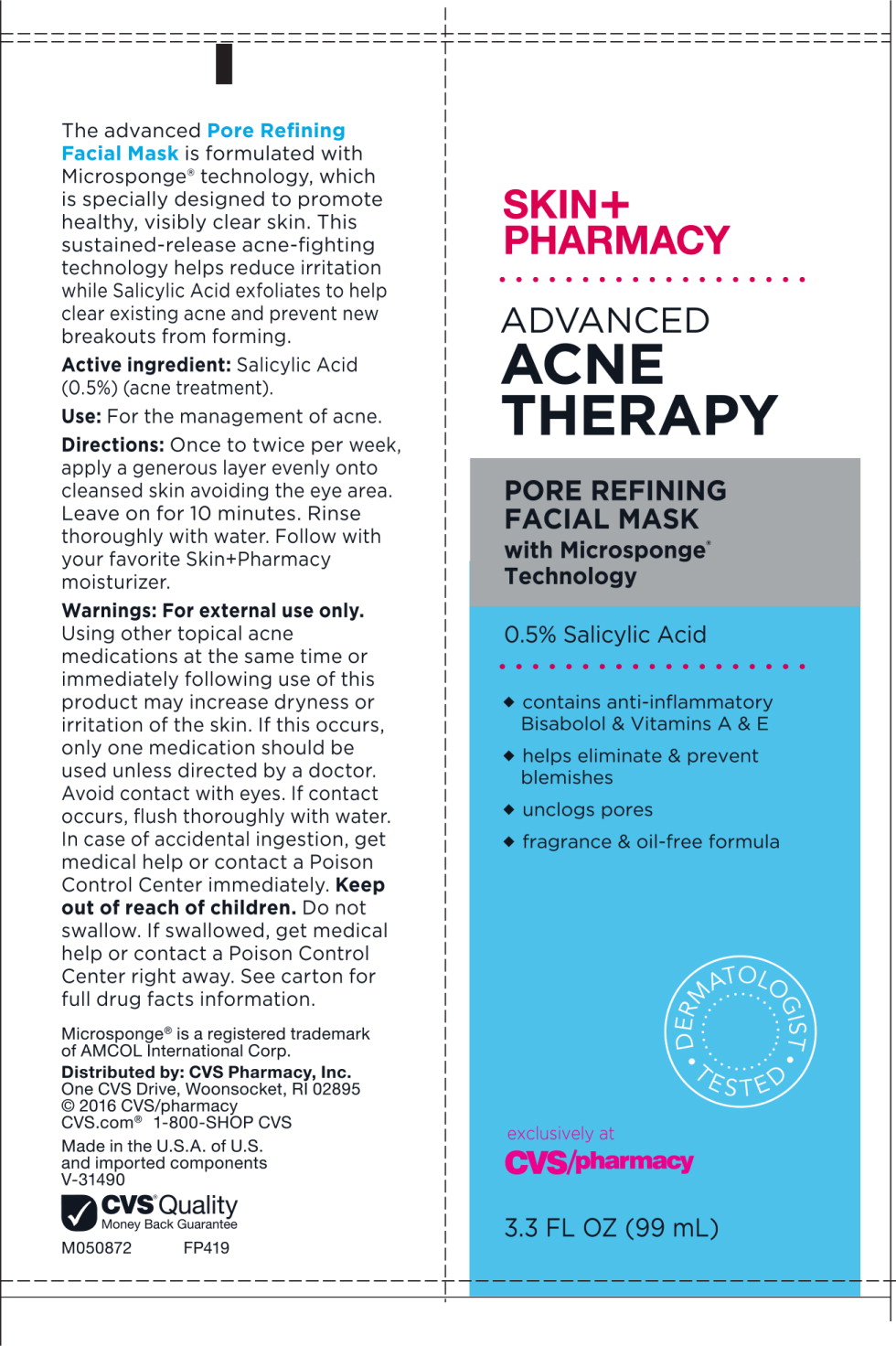 DRUG LABEL: SKIN PHARMACY ADVANCED ACNE THERAPY PORE REFINING FACIAL MASK
NDC: 68634-058 | Form: LIQUID
Manufacturer: AMCOL Health & Beauty Solutions, Inc. DBA
Category: otc | Type: HUMAN OTC DRUG LABEL
Date: 20160611

ACTIVE INGREDIENTS: salicylic acid 5 g/2 mL
INACTIVE INGREDIENTS: water; kaolin; glycerin; bentonite; butylene glycol; cetostearyl alcohol; methyl methacrylate/glycol dimethacrylate crosspolymer; cocamidopropyl betaine; peg-100 stearate; magnesium aluminum silicate; glyceryl monostearate; phenoxyethanol; polyoxyl 20 cetostearyl ether; xanthan gum; chlorphenesin; caffeine; ethylhexylglycerin; edetate disodium; citric acid monohydrate; sodium hydroxide; .alpha.-tocopherol acetate; vitamin a palmitate; ascorbyl palmitate; levomenol

SKIN+PHARMACY
ADVANCED ACNE THERAPY
PORE REFINING FACIAL MASK

HBS Code (Labeler): FP41901-99.1

Distributor: CVS Pharmacy, Inc.

Human OTC Drug

Active Ingredients: Salicylic Acid 0.5%

CARTON TEXT

________________________________________________________

SKIN+PHARMACY

ADVANCED ACNE THERAPY

PORE REFINING SKIN MASK with Microsponge® Technology

0.5% Salicylic Acid

- contains anti-inflammatory Bisabolol & Vitamins A & E
- helps eliminate & prevent blemishes
- unclogs pores
- fragrance & oil-free formula

DERMATOLOGIST TESTED

exclusively at CVS/pharmacy

Actual Product Size on Side Panel

3.3 FL OZ (99 mL)

The advanced Pore Refining Facial Mask is formulated with Microsponge® technology, which is specially designed to promote healthy, visibly clear skin. This sustained-release acne-fighting technology helps reduce irritation while Salicylic Acid exfoliates to help clear existing acne and prevent new breakouts from forming. This mask contains Kaolin and Bentonite Clay to help draw out dirt and impurities combined with anti-inflammatory Bisabolol and antioxidants to help provide free radical protection, leaving your skin feeling clean, smooth, and refreshed with continued use.

Key Benefits:

- helps eliminate existing blemishes
- helps prevent new breakouts from forming
- unclogs pores
- oil-free formula
- fragrance free

Daily Regimen:

For best results, use this product with the full Skin+Pharmacy Advanced Acne Therapy regimen.

1. Cleanse
  Clarifying Daily Cleanser
  Gentle Exfoliating Scrub
2. Moisturize
  Active Clearing Lotion
3. Treat
  Pore Refining Facial Mask
  Spot Treatment
  Targeted Treatment Wipes
  Salicylic Acid Lotion
  Mattifying Lotion

Skin+Pharmacy Advanced Acne Therapy is an innovative line of clinically tested skin care products that help reduce the appearance of acne. These products, exclusive to CVS/pharmacy, are less irritating to skin, yet powerful enough to treat breakouts and unclog pores. Let Skin+Pharmacy help improve your appearance toward a clear, acne-free complexion.

Actual Size

Drug Facts

Active Ingredient

Salicylic Acid 0.5%

Purpose

Acne

Use

for the management of acne

Warnings

For external use only

When using this product

- using other topical acne medications at the same time or immediately following use of this product may increase dryness or irritation of the skin. If this occurs, only one medication should be used unless directed by a doctor.
- avoid contact with eye. if contact occurs, flush thoroughly with water.
- In case of accidental ingestion, get medical help or contact a Poison Control Center immediately.

Keep out of reach of children. Do not swallow. If swallowed, get medical help or contact a Poison Control Center right away.

Directions

- Once to twice per week, apply a generous layer evenly onto cleansed skin avoiding the eye area.
- Leave on for 10 minutes.
- Follow with your favorite Skin+Pharmacy moisturizer.

Inactive ingredients

Water, Kaolin, Glycerin, Bentonite, Butylene Glycol, Cetearyl Alcohol, Methyl Methacrylate/Glycol Dimethacrylate Crosspolymer, Cocamidopropyl Betaine, PEG-100 Stearate, Magnesium Aluminum Silicate, Glyceryl Stearate, Phenoxyethanol, Ceteareth-20, Xanthan Gum, Chlorphenesin, Caffeine, Ethylhexylglycerin, Disodium EDTA, Citric Acid, Sodium Hydroxide, Tocopheryl Acetate, Retinyl Palmitate, Ascorbyl Palmitate, Bisabolol.

Microsponge® is a registered trademark of AMCOL International Corp.

Save carton for complete labeling since all warnings are not included on the inner package.

Distributed by: CVS Pharmacy, Inc.

One CVS Drive, Woonsocket, RI 02895

© 2016 CVS/pharmacy

CVS.com® 1-800-SHOP CVS

Made in the U.S.A. of U.S. and foreign components

V-13649

CVS® Quality
Money Back Guarantee

M050873CP
FP419
#742825

________________________________________________________

end of text

160611

AMCOL Health & Beauty Solutions, Inc. DBA AMCOL Household and Personal Care

301 Laser Lane Lafayette, LA 70507 | www.amcolhpc.com

lauren.haase@mineralstech.com

Principal Display Panel - 5 g/2 mL Carton Label

SKIN +
PHARMACY

ADVANCED
ACNE
THERAPY

PORE REFINING
FACIAL MASK

with Microsponge*
Technology

0.5% Salicylic Acid

- contains anti-inflammatory
  Bisabolol & Vitamins A & E
- helps eliminate & prevent
  blemishes
- unclogs pores
- fragrance- & oil-free formula

exclusively at

CVS/pharmacy

Actual Size Product
on Side Panel

3.3 FL OZ (99 mL)

Principal Display Panel - 5 g/2 mL Tube Label

SKIN +
PHARMACY

ADVANCED
ACNE
THERAPY

PORE REFINING
FACIAL MASK

with Microsponge*
Technology

0.5% Salicylic Acid

- contains anti-inflammatory
  Bisabolol & Vitamins A & E
- helps eliminate & prevent
  blemishes
- unclogs pores
- fragrance- & oil-free formula

exclusively at

CVS/pharmacy

Actual Size Product
on Side Panel

3.3 FL OZ (99 mL)